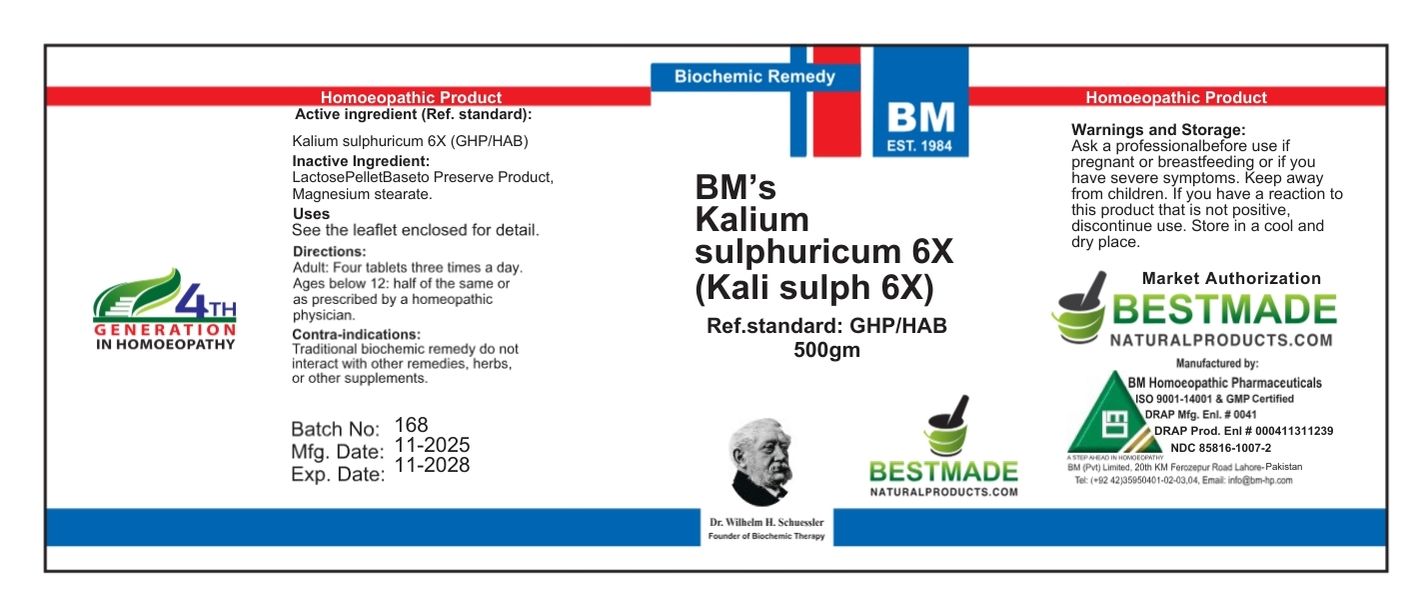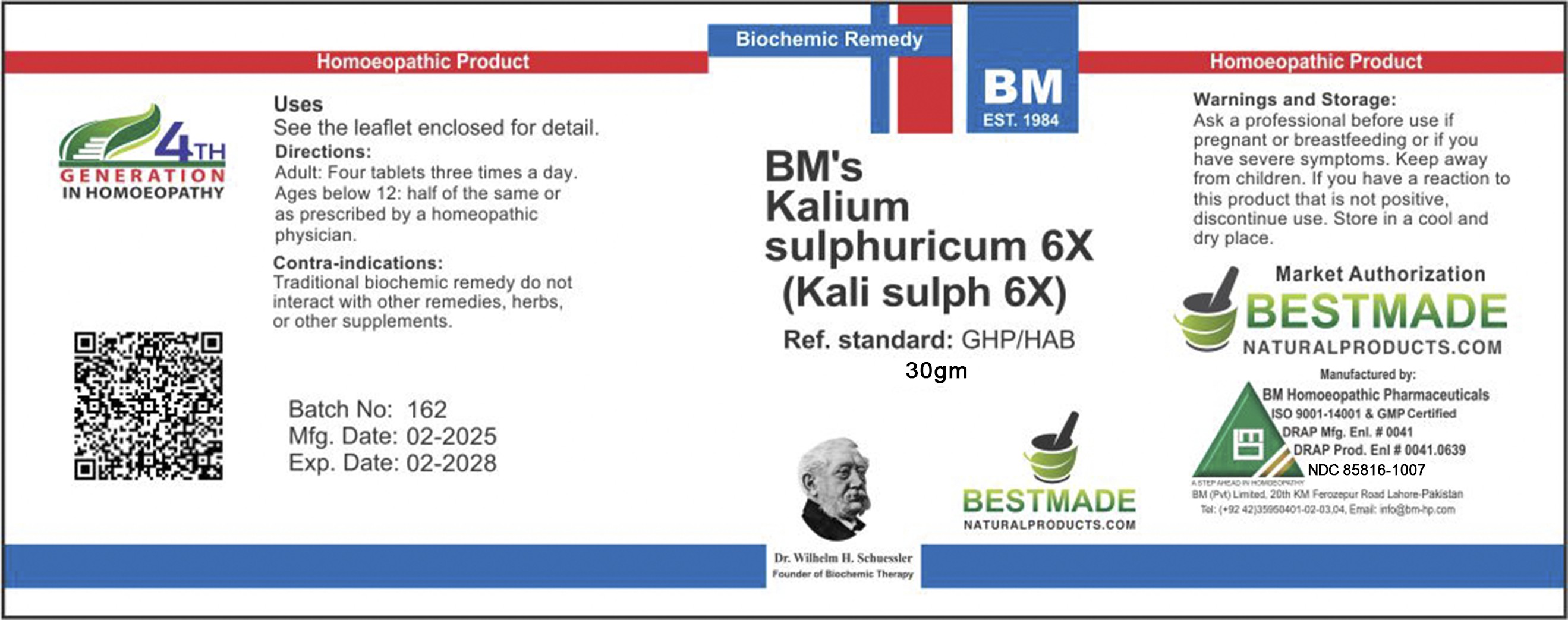 DRUG LABEL: BM Kali Sulph
NDC: 85816-1007 | Form: TABLET
Manufacturer: BM Private Limited
Category: homeopathic | Type: HUMAN OTC DRUG LABEL
Date: 20251202

ACTIVE INGREDIENTS: POTASSIUM SULFATE 6 [hp_X]/60 mg
INACTIVE INGREDIENTS: MAGNESIUM STEARATE 1.25 mg/60 mg; LACTOSE 58.6 mg/60 mg

BM Kali Sulph 6X

ACTIVE INGREDIENT

Kalium Sulphuricum

Inactive ingredients: Lactose; MAGNESIUM STEARATE

Warnings and Storage:

Ask a professional before use if pregnant or breastfeeding or if you have severe symptoms. Keep away from children. If you have a reaction to this product that is not positive, discontinue use. Store in a cool and dry place.

KEEP OUT OF REACH OF CHILDREN

Warnings and Storage:

Ask a professional before use if pregnant or breastfeeding or if you have severe symptoms. Keep away from children. If you have a reaction to this product that is not positive, discontinue use. Store in a cool and dry place.

CONTRAINDICATIONS

Contra-indications:
Traditional biochemic remedy do not interact with other remedies, herbs, or other supplements.

Directions:
Adult: Four tablets three times a day.
Ages below 12: half of the same or as prescribed by a homeopathic physician.

Uses
See the leaflet enclosed for detail.

Uses
See the leaflet enclosed for detail.

Package 1 (30g)

Package 2 (500g)